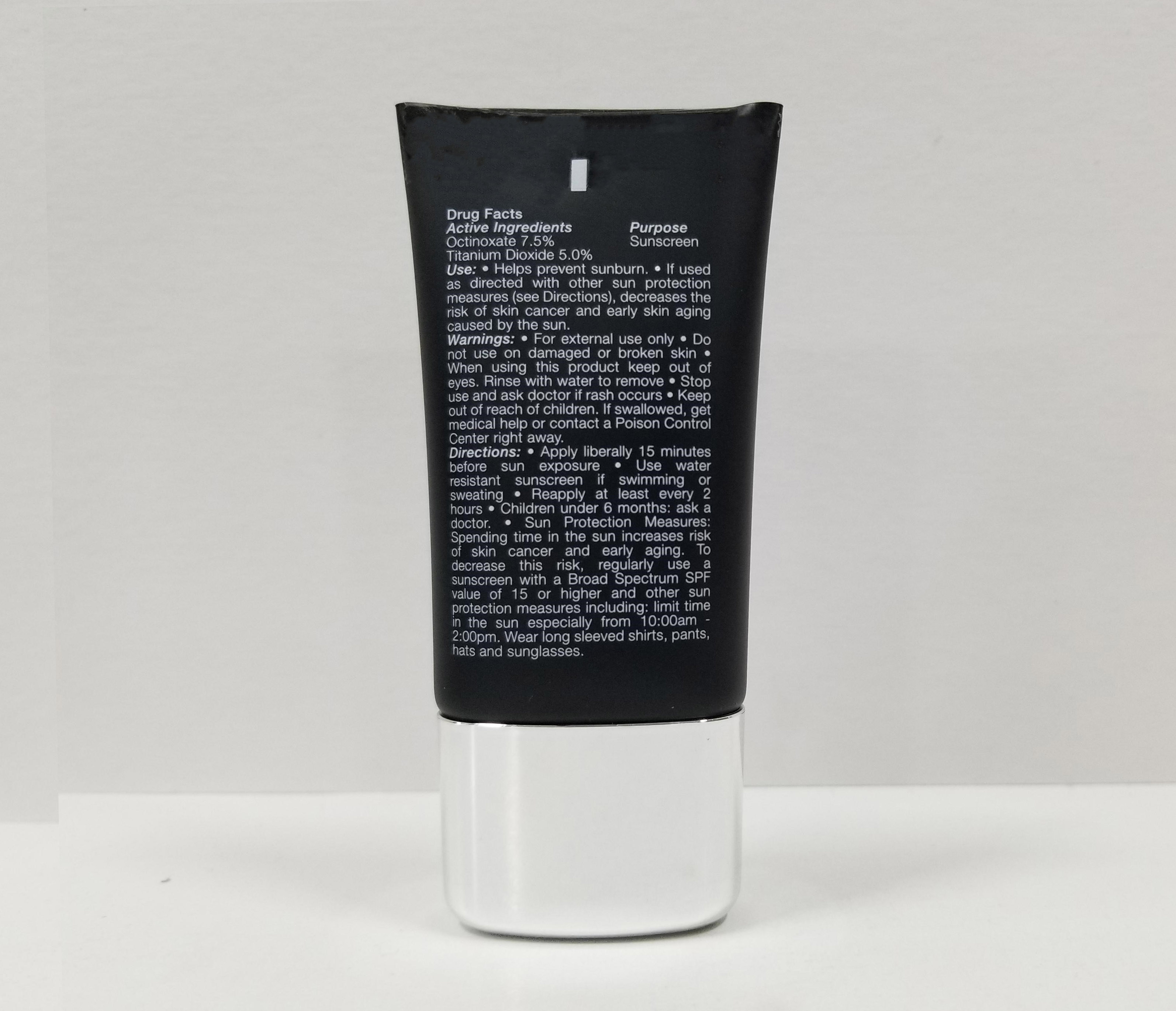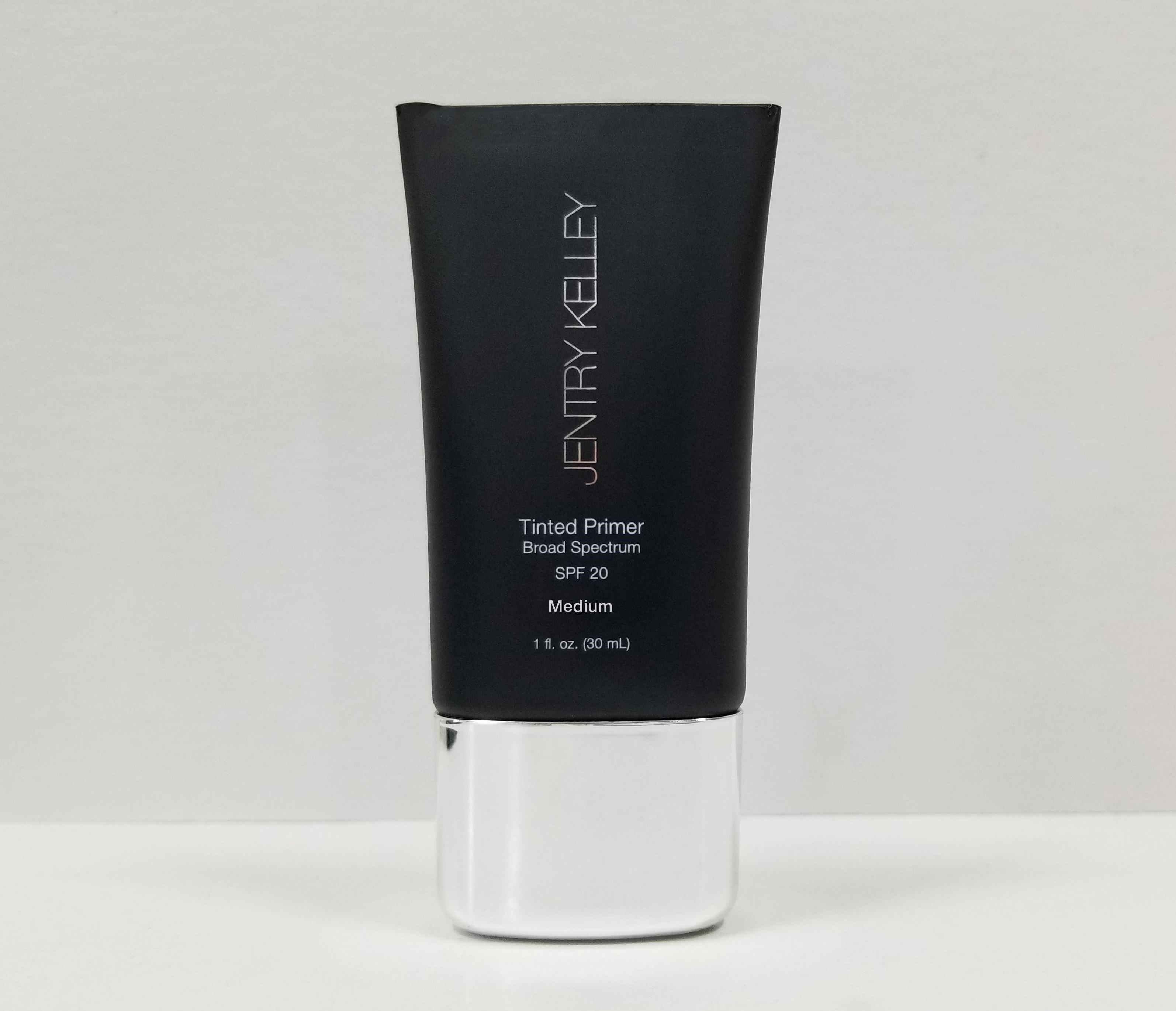 DRUG LABEL: JENTRY KELLEY TINTED PRIMER BROAD SPECTRUM SPF 20- MEDIUM
NDC: 84179-204 | Form: CREAM
Manufacturer: Jentry Kelley
Category: otc | Type: HUMAN OTC DRUG LABEL
Date: 20240416

ACTIVE INGREDIENTS: OCTINOXATE 7.5 g/36 mL; TITANIUM DIOXIDE 5 g/36 mL
INACTIVE INGREDIENTS: CYCLOMETHICONE 5; WATER; ISODODECANE; TOCOPHEROL; CERAMIDE NP; CAPRYLYL GLYCOL; HEXYLENE GLYCOL; SODIUM DEHYDROACETATE; EDETATE DISODIUM; FERROSOFERRIC OXIDE; FERRIC OXIDE RED; LICORICE; HYALURONIC ACID (NON-ANIMAL STABILIZED); NYLON-12; PHENYL TRIMETHICONE; DISTEARDIMONIUM HECTORITE; BUTYLATED HYDROXYTOLUENE; FERRIC OXIDE YELLOW; BUTYLENE GLYCOL; PEG-10 DIMETHICONE (200 CST); ALUMINUM HYDROXIDE; .ALPHA.-TOCOPHEROL ACETATE, D-; VITAMIN A PALMITATE; SODIUM CHLORIDE; STEARIC ACID; TETRAHEXYLDECYL ASCORBATE; BORON NITRIDE; METHICONE (20 CST); TRIETHOXYCAPRYLYLSILANE; OLIVE OIL; PHENOXYETHANOL; BIS-PEG/PPG-14/14 DIMETHICONE; MICA; NYLON 612 (MW 14000)

JENTRY KELLEY TINTED PRIMER BROAD SPECTRUM SPF 20- MEDIUM

Actives

Octinoxate 7.5%

Titanium Dioxide 5.00%

Purpose

Sunscreen active

USE

Helps prevent sunburn.
If used as directed with other sun protection measures (see Directions), decreases the risk of skin cancer and early skin aging caused by the sun.

WARNINGS

For external use only
Do not use on damaged or broken skin
When using this product keep out of eyes. Rinse with water to remove.

Stop use and ask a doctor if rash occurs.

Keep out of reach of children. If swallowed, get medical help or contact a Poison Control Center right away.

DIRECTIONS

Apply liberally 15 minutes before sun exposure.
Use water resistant sunscreen if swimming or sweating.

Reapply at least every 2 hours.

Children under 6 months: ask a doctor.
Sun Protection Measures: Spending time in the sun increases risk of skin cancer and early aging. To decrease this risk, regularly use a sunscreen with a Broad Spectrum SPF value of 15 or higher and other sun protection measures including: Limit time in the sun especially from 10:00 am - 2:00 pm. Wear long sleeved shirts, pants, hats and sunglasses.

INACTIVE INGREDIENTS

Water, Cyclopentasiloxane, Butylene Glycol, Titanium Dioxide, Zinc Oxide, Octyldodecyl Neopentanoate, PEG/PPG-18/18 Dimethicone, Dimethicone, Tocopherol, Tetrahexyldecyl Ascorbate, Retinyl Palmitate, Camellia Sinensis Leaf Extract, Chamomilla Recutita (Matricaria) Flower Extract, Ginkgo Biloba Leaf Extract, Panax Ginseng Root Extract, Octyldodecanol, Boron Nitride, Dextrin Palmitate, Palmitic Acid, Methicone, Stearic Acid, Magnesium Chloride, Potassium Chloride, Sodium Chloride, Zinc Chloride, Magnesium Ascorbyl Phosphate, Sodium Hyaluronate, Phytantriol, Glycerin, Triethoxycaprylylsilane, Lysine, Aluminum Hydroxide, Disodium EDTA, Hexylene Glycol, Potassium Sorbate, Sodium Dehydroacetate, Caprylyl Glycol, Phenoxyethanol

MAY CONTAIN (+/-):

Mica, Titanium Dioxide (CI 77891), Iron Oxides (CI 77491, CI 77492, CI 77499)

OTHER INFORMATION

Protect this product from excessive heat and direct sun.

RECENT MAJOR CHANGES

Label update